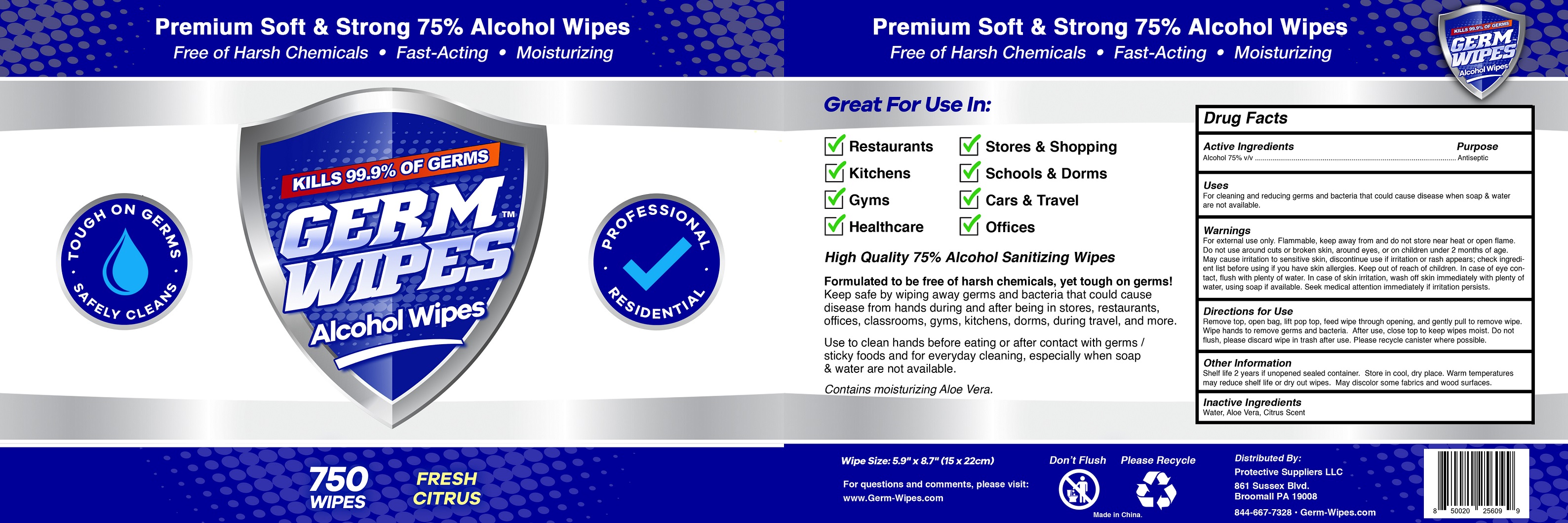 DRUG LABEL: Alcohol Wipes
NDC: 79953-750 | Form: CLOTH
Manufacturer: Protective Suppliers LLC
Category: otc | Type: HUMAN OTC DRUG LABEL
Date: 20200806

ACTIVE INGREDIENTS: ALCOHOL 75 mL/100 g
INACTIVE INGREDIENTS: ALOE VERA LEAF; PECTIN, CITRUS; WATER

79953-750 Alcoho wipes Ningbo Chenxing Daily Necessities Co., Ltd.

Active Ingredient(s)

Alcohol 75% v/v. Purpose: Antiseptic

Purpose

Antiseptic, Alcohol wipes

Use

For cleaning and reducing germs and bacteria that could cause disease when soap & water are not available.

Warnings

For external use only. Flammable. Keep away from and do not store near heat or open flame.Do not use around cuts or broken skin, around eyes, or on children under 2 months of age. May cause irritation to sensitive skin,discontinue use if irritation or rash appears; check ingredient list before using if you have skin allergies. Keep out of reach of children. In case of eye contact, flush with plenty of water, using soap if available. Seek medical attention immediately if irritation persists.

Do not use

- in children less than 2 months of age
- on open skin wounds

When using this product keep out of eyes, ears, and mouth. In case of contact with eyes, rinse eyes thoroughly with water.
Stop use and ask a doctor if irritation or rash occurs. These may be signs of a serious condition.
Keep out of reach of children. If swallowed, get medical help or contact a Poison Control Center right away.

Stop use and ask a doctor if irritation or rash occurs. These may be signs of a serious condition.

Keep out of reach of children. If swallowed, get medical help or contact a Poison Control Center right away.

Directions

Remove top, remove foil,lift pop top,feed wipe through opening, and gently pull to remove wipe. Gently wipe hands to remove germs and becteria. After use, close top to keep wipes moist. Do not flush, please discard wipe in trash after use. Please recycle canister where possible.

Other information

Shelf life 2 years if unopened sealed container. Store in cool, dry place. Warm temperatures may reduce shelf life or dry out wipes. May discolor some fabrics and wood surface.

Inactive ingredients

Water, Aloe vera, Citrus Scent.

Package Label - Principal Display Panel

750 wipes NDC: 79953-750-01